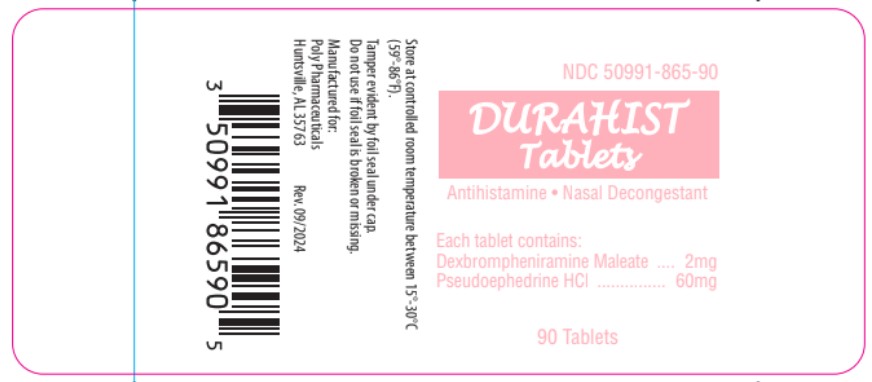 DRUG LABEL: Durahist
NDC: 50991-865 | Form: TABLET
Manufacturer: Poly Pharmaceuticals, Inc.
Category: otc | Type: HUMAN OTC DRUG LABEL
Date: 20251230

ACTIVE INGREDIENTS: PSEUDOEPHEDRINE HYDROCHLORIDE 60 mg/1 1; DEXBROMPHENIRAMINE MALEATE 2 mg/1 1
INACTIVE INGREDIENTS: FD&C RED NO. 40 ALUMINUM LAKE; CELLULOSE, MICROCRYSTALLINE; SODIUM STARCH GLYCOLATE TYPE A; MAGNESIUM STEARATE; FD&C YELLOW NO. 6

Durahist

Purpose
Dexbrompheniramine Maleate .................. Antihistamine
Pseudoephedrine HCI ................... Nasal Decongestant

Active ingredients
(in each tablet)
Dexbrompheniramine Maleate 2mg
Pseudoephedrine HCI 60mg

Uses

Temporarily relieves these symptoms due to hay fever (allergic rhinitis) or upper respiratory allergies:

- runny nose
- sneezing
- itching of the nose or throat
- itchy, watery eyes
- nasal congestion
- reduces swelling of nasal passages

WARNINGS

Do not exceed recommended dosage.

Do not use this product if you are now taking a prescription monoamine oxidase inhibitor (MAOI) (certain drugs for depression,psychiatric, or emotional conditions, or Parkinson's disease), or for 2 weeks after stopping the MAOI drug. If you do not know if your prescription drug contains an MAOI, ask a doctor or pharmacist before taking this product.

Ask a doctor before use if you have

- a breathing problem such as emphysema or chronic bronchitis
- glaucoma
- trouble urinating due to enlargement of the prostate gland
- heart disease
- high blood pressure
- thyroid disease
- diabetes

Ask a doctor or pharmacist before use if you are taking sedatives or tranquilizers.

When using this product

- excitability may occur, especially in children
- may cause drowsiness
- avoid alcoholic drinks
- alcohol, sedatives, and tranquilizers may increase the drowsiness effect
- use caution when driving a motor vehicle or operating machinery

Stop use and ask a doctor if

- nervousness, dizziness, or sleeplessness occur
- symptoms do not improve within 7 days or are accompanied by fever

PREGNANCY OR BREAST FEEDING

If pregnant or breast-feeding, ask a health professional before use.

Keep out of reach of children.
In case of overdose, get medical help or contact a Poison Control Center right away.

Directions

Adults and children 12 years of age and over: | 1 tablet every 4 to 6 hours, not to exceed 4 tablets in 24 hours.
Children 6 to under 12 years of age: | 1/2 tablet every 4 to 6 hours, not to exceed 2 tablets in 24 hours.
Children under 6 years of age: | Consult a doctor.

Other information

Store at 15° - 30°C (59° - 86°F).

Supplied in a tight, light-resistant container with a child-resistant cap.

Durahist Tablets are pink caplet shaped, scored tablets, debossed "Poly" bisect "865" on one side and plain on the other.

Inactive ingredients

Lake Blend Red, Magnesium Stearate, Microcrystalline Cellulose and Sodium Starch Glycolate.

Questions?

Call 1-800-882-1041

Manufactured for:
Poly Pharmaceuticals
Quitman, MS 39355

Rev. 09/2024

Product Packaging

The packaging below represents the labeling currently used.

Principal display panel for 90 tablets label:

NDC 50991-865-90